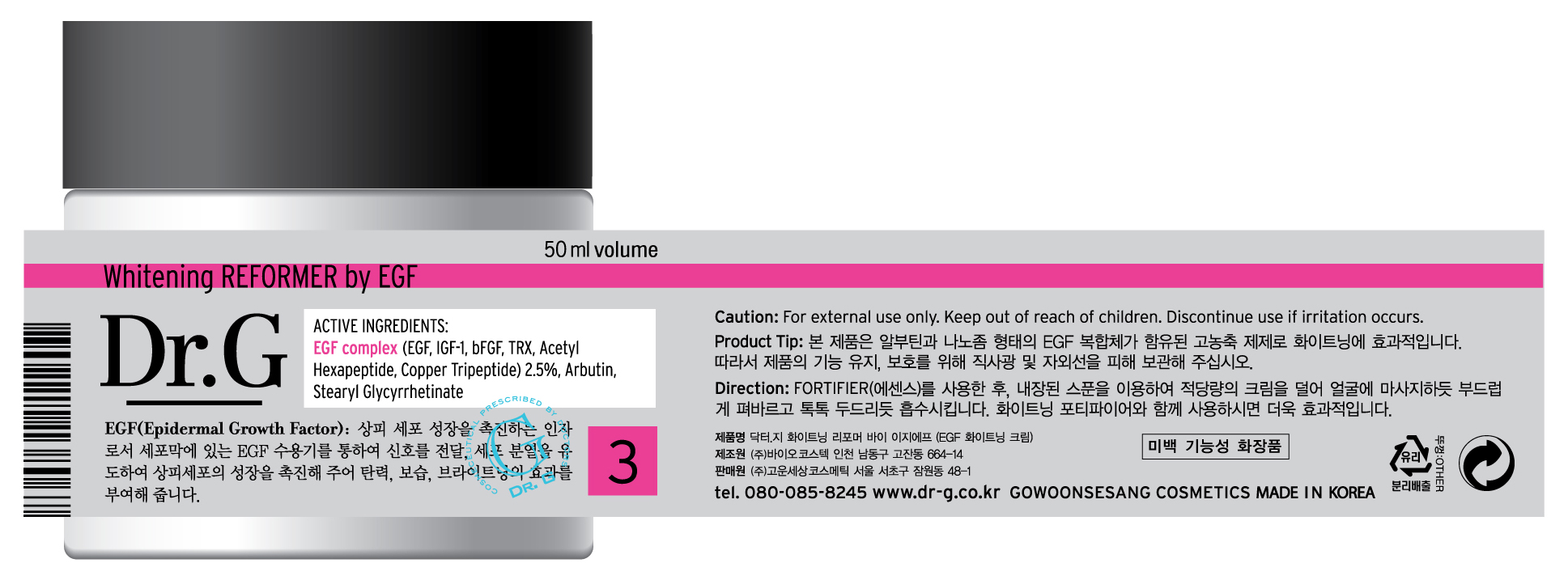 DRUG LABEL: Dr G Whitening REFORMER by EGF
NDC: 43948-4002 | Form: CREAM
Manufacturer: The Doctor's Cosmetic Inc
Category: otc | Type: HUMAN OTC DRUG LABEL
Date: 20091001

ACTIVE INGREDIENTS: ARBUTIN 1 mL/50 mL; DIMETHICONE 2 mL/50 mL

ACTIVE INGREDIENTS:

Dimethicone, EGF complex (EGF, IGF-1, bFGF, TRX, Acetyl Hexapeptide, Copper Tripeptide) 2.5%, Arbutin, Stearyl Glycyrrhetinate

KEEP OUT OF REACH OF CHILDREN

Caution: For external use only. Keep out of reach of children. Discontinue use if irritation occurs.

WHEN USING

DIRECTION OF USE:

After using Fortifier(essence) take an appropriate amount of cream using the enclosed spoon and gently spread on face as if massaging. Tap lightly for absorption. For better results, use with whitening Fortifier.

PACKAGE LABEL

Label4c